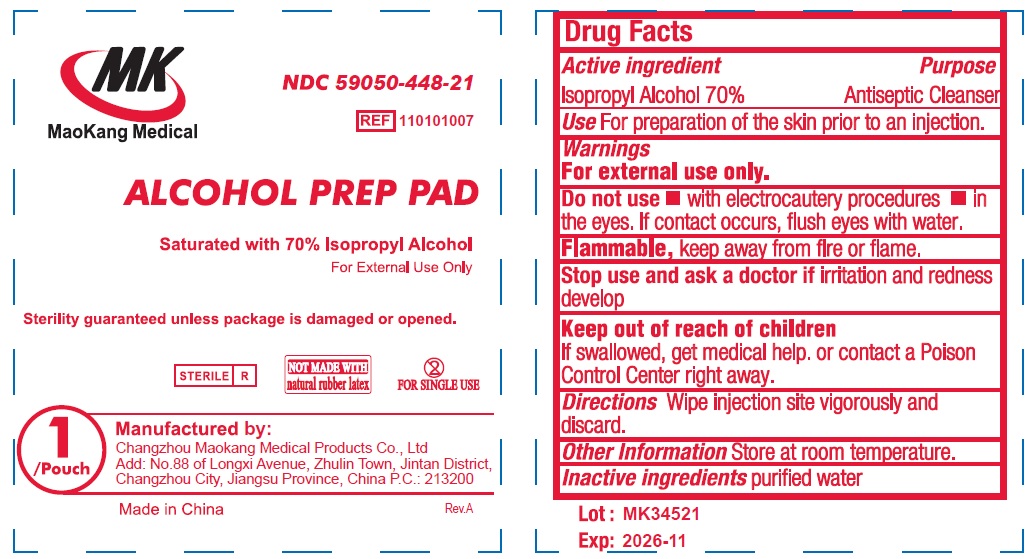 DRUG LABEL: MK Alcohol Prep Pads Large
NDC: 59050-448 | Form: LIQUID
Manufacturer: Changzhou Maokang Medical Products Co., Ltd
Category: otc | Type: HUMAN OTC DRUG LABEL
Date: 20251120

ACTIVE INGREDIENTS: ISOPROPYL ALCOHOL 70 mL/100 mL
INACTIVE INGREDIENTS: WATER

MK Alcohol Prep Pads Large Non-Sterile

Active ingredient

Isopropyl Alcohol, 70%

Purpose

Antiseptic Cleanser

Use

For preparation of the skin prior to an injection.

Warnings

For external use only. Flammable, keep away from fire or flame.

Do not use

- with electrocautery procedures
- in the eyes. If contact occurs, flush eyes with water.

Stop use and ask a doctor if

irritation or redness develop

Keep out of reach of children.

If swallowed, get medical help, or contact a Poison Control center right away.

Directions

Wipe injection site vigorously and discard.

Other Information

Store at room temperature.

Inactive ingredients

purified water